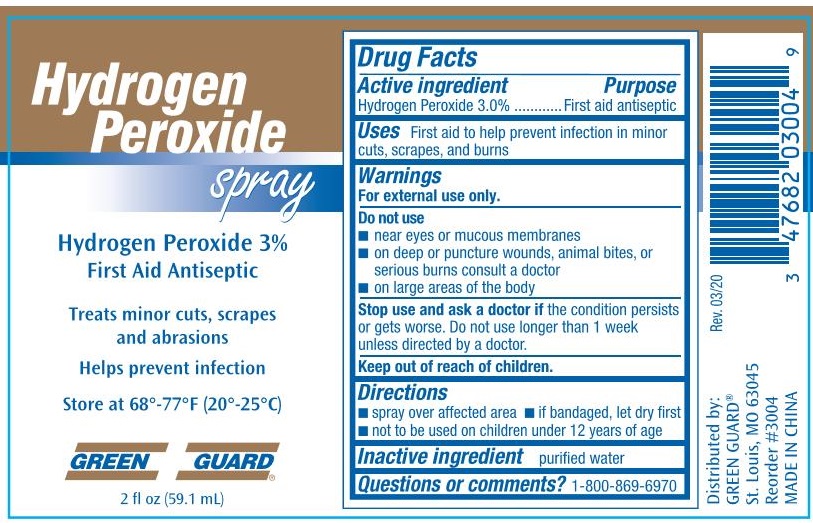 DRUG LABEL: Green Guard Hydrogen Peroxide
NDC: 47682-334 | Form: SPRAY
Manufacturer: Unifirst First Aid Corporation
Category: otc | Type: HUMAN OTC DRUG LABEL
Date: 20250908

ACTIVE INGREDIENTS: HYDROGEN PEROXIDE 30 mL/1 L
INACTIVE INGREDIENTS: WATER

Grenn Guard First Aid & Safety Hydrogen Peroxide Spray

Active ingredient

Hydrogen Peroxide 3.0%

Purpose

First aid antiseptic

Uses

First aid to help prevent infection in minor cuts, scrapes and burns

Warnings

For external use only.

Do not use

- near eyes or mucous membranes
- on deep or puncture wounds, animal bites, or serious burns consult a doctor
- on large areas of the body

Stop use and ask a doctor if the condition persists or gets worse. Do not use longer than 1 week unless directed by a doctor.

Keep out of reach of children.

Directions

- spray over affected area
- if bandaged, let dry first
- not to be used on children under 12 years of age

Inactive ingredient

purified water

Questions or comments? 1-800-869-6970

Green Guard Hydrogen Peroxide Spray Label

Hydrogen Peroxide Spray

Hydrogen Peroxide 3%

First Aid Antiseptic

Treats minor cuts, scrapes and abrasions

Helps prevent infection

Store at 68°-77°F (20°-25°C)

Green Guard®

2 fl oz (59.1 mL)